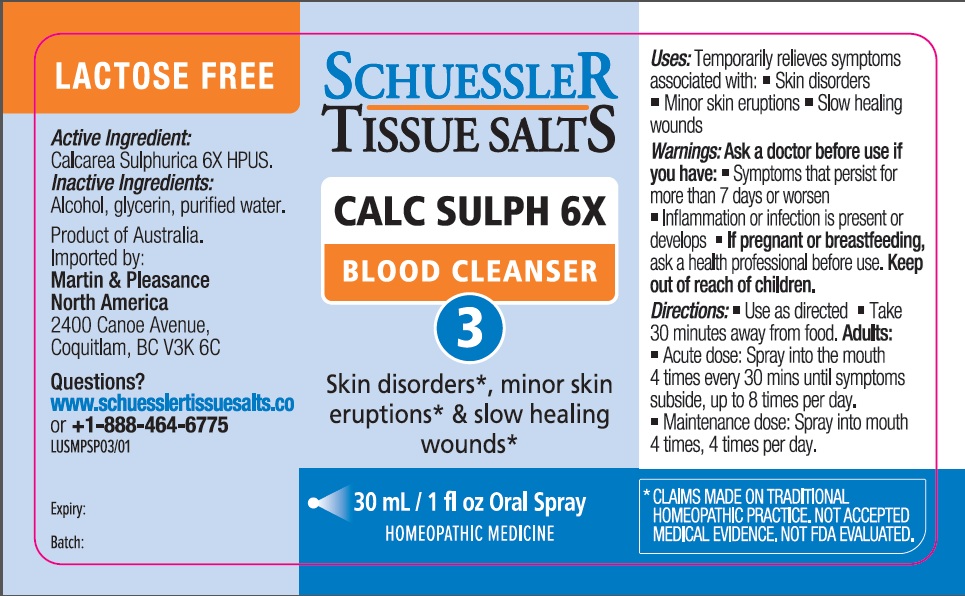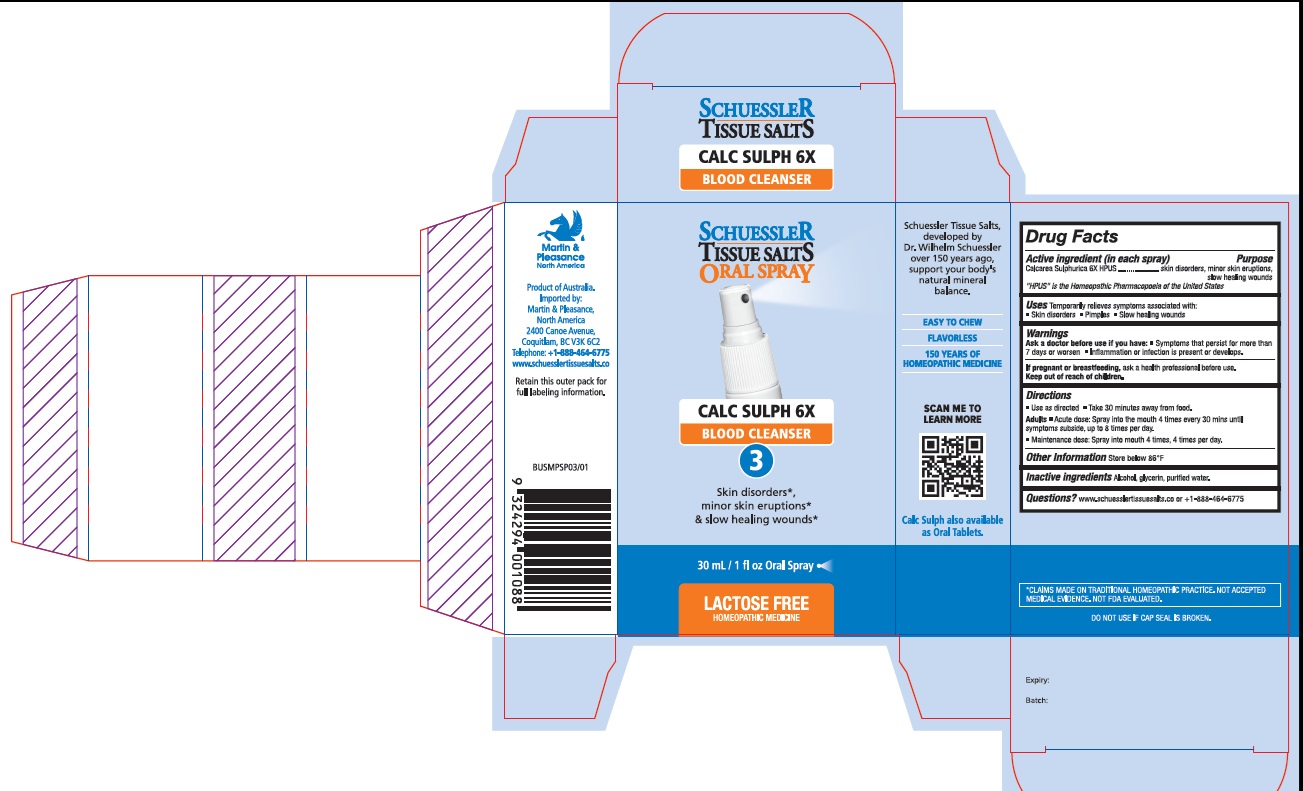 DRUG LABEL: Schuessler Tissue Salts Calc Sulph Blood Cleanser 3
NDC: 84999-003 | Form: SPRAY
Manufacturer: Martin & Pleasance Pty Ltd
Category: homeopathic | Type: HUMAN OTC DRUG LABEL
Date: 20250701

ACTIVE INGREDIENTS: CALCIUM SULFATE DIHYDRATE 6 [hp_X]/30 mL
INACTIVE INGREDIENTS: ALCOHOL; GLYCERIN; WATER

Active Ingredients Purpose

Calcarea Sulphurica 6X HPUS skin disorders, minor skin eruptions,slow healing

wounds

" HPUS" is the Homeopathic Pharmacopoeia of the United States

Uses

- Temporarily relieves symptoms associated with:
- Skin disorders
- Minor skin eruptions
- Slow healing wounds

Warnings

Ask a doctor before use if you have:

- Symptoms that persist for more than 7 days or worsen
- Inflammation or infection is present or develops.

If pregnant or breastfeeding, ask a health professional before use. Keep out of reach of children.

Directions

- Use as directed
- Take 30 minutes away from food.

Adults

- Acute dose: Spray into the mouth 4 times every 30 mins until symptoms subside, up to 8 times per day.
- Maintenance dose: Spray into mouth 4 times, 4 times per day.

Other Information

Store below 86"F

Inactive Ingredients

Alcohol, glycerin, purified water.

Questions?www.schuesslertissuesalts.co or + 1-888-464-6775